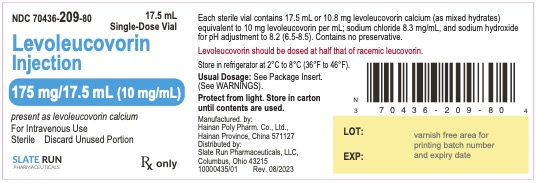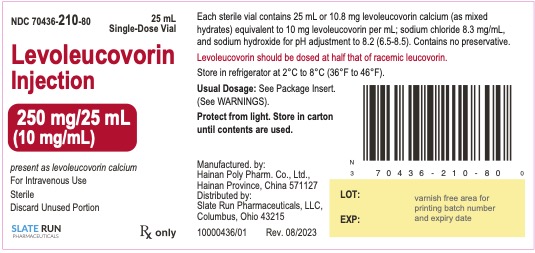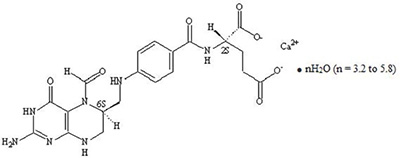 DRUG LABEL: LEVOLEUCOVORIN CALCIUM
NDC: 70436-209 | Form: INJECTION, SOLUTION
Manufacturer: Slate Run Pharmaceuticals
Category: prescription | Type: HUMAN PRESCRIPTION DRUG LABEL
Date: 20230829

ACTIVE INGREDIENTS: LEVOLEUCOVORIN CALCIUM 10 mg/1 mL
INACTIVE INGREDIENTS: WATER; SODIUM CHLORIDE 8.3 mg/1 mL; SODIUM HYDROXIDE

HIGHLIGHTS OF PRESCRIBING INFORMATION

These highlights do not include all the information needed to use LEVOLEUCOVORIN INJECTION safely and effectively. See full prescribing information for LEVOLEUCOVORIN INJECTION.
Levoleucovorin injection, for intravenous use
Initial U.S. Approval: 1952 (d,l-leucovorin)

1 INDICATIONS AND USAGE

Levoleucovorin injection is a folate analog indicated for:

- Rescue after high-dose methotrexate therapy in adult and pediatric patients with osteosarcoma. (1)
- Diminishing the toxicity associated with overdosage of folic acid antagonists or impaired methotrexate elimination in adult and pediatric patients. (1)
- Treatment of adults with metastatic colorectal cancer in combination with fluorouracil. (1)

Limitations of Use:

Levoleucovorin injection is not indicated for the treatment of pernicious anemia and megaloblastic anemia secondary to lack of vitamin B12, because of the risk of progression of neurologic manifestations despite hematologic remission. (1)

2 DOSAGE AND ADMINISTRATION

For intravenous administration only. Do not administer intrathecally. (2.1)

Rescue After High-Dose Methotrexate Therapy

- Rescue recommendations are based on methotrexate dose of 12 grams/m^2administered by intravenous infusion over 4 hours. Initiate rescue at a dose of 7.5 mg (approximately 5 mg/m^2) every 6 hours, 24 hours after the beginning of methotrexate infusion. (2.3)
- Continue until the methotrexate level is below 5 x 10^-8M (0.05 micromolar). Adjust dose if necessary based on methotrexate elimination; refer to Full Prescribing Information. (2.3)

Overdosage of Folic Acid Antagonists or Impaired Methotrexate Elimination

- Start as soon as possible after methotrexate overdosage or within 24 hours of delayed methotrexate elimination. (2.4)
- Administer levoleucovorin injection 7.5 mg (approximately 5 mg/m^2) intravenously every 6 hours until methotrexate level is less than 5 x 10^-8M (0.05 micromolar). (2.4)

Metastatic Colorectal Cancer in Combination with Fluorouracil

- The following regimens have been used for the treatment of colorectal cancer:
  - Levoleucovorin injection 100 mg/m^2by intravenous injection over a minimum of 3 minutes, followed by fluorouracil 370 mg/m^2once daily for 5 consecutive days. (2.5)
  - Levoleucovorin injection 10 mg/m^2by intravenous injection followed by fluorouracil 425 mg/m^2once daily for 5 consecutive days. (2.5)
- Administer Fluorouracil and levoleucovorin injection separately to avoid the formation of precipitate.
- The above five-day courses may be repeated every 4 weeks for 2 courses, then every 4 to 5 weeks, if the patient has recovered from toxicity from the prior course.
- Do not adjust levoleucovorin injection dosage for toxicity. (2.5)

3 DOSAGE FORMS AND STRENGTHS

- Injection: 175 mg per 17.5 mL (10 mg per mL) or 250 mg per 25 mL (10 mg per mL) in a single-dose vial (3)

4 CONTRAINDICATIONS

Patients who have had severe hypersensitivity reactions to leucovorin products, folic acid or folinic acid. (4)

5 WARNINGS AND PRECAUTIONS

- Hypercalcemia:Due to calcium content, inject no more than 16 mL (160 mg) of levoleucovorin solution intravenously per minute. (5.1)
- Increased Gastrointestinal Toxicities with Fluorouracil: Do not initiate or continue therapy with levoleucovorin and fluorouracil in patients with symptoms of gastrointestinal toxicity until symptoms have resolved. Monitor patients with diarrhea until it has resolved as rapid deterioration leading to death can occur. (5.2, 7)
- Drug Interaction with Trimethoprim-Sulfamethoxazole: Increased rates of treatment failure and morbidity with concomitant use of d,l-leucovorin with trimethoprim-sulfamethoxazole for Pneumocystis jiroveci pneumonia in patients with HIV. (5.3)

6 ADVERSE REACTIONS

- The most common adverse reactions (≥20%) in patients receiving high-dose methotrexate therapy with levoleucovorin rescue are stomatitis and vomiting. (6.1)
- The most common adverse reactions (>50%) in patients receiving levoleucovorin in combination with fluorouracil for metastatic colorectal cancer are stomatitis, diarrhea, and nausea. (6.1)

To report SUSPECTED ADVERSE REACTIONS, contact Slate Run Pharmaceuticals at 1-800-341-9214 or FDA at 1-800-FDA-1088 or www.fda.gov/medwatch.

FULL PRESCRIBING INFORMATION

1 INDICATIONS AND USAGE

Levoleucovorin injection is indicated for:

- rescue after high-dose methotrexate therapy in adult and pediatric patients with osteosarcoma.
- diminishing the toxicity associated with overdosage of folic acid antagonists or impaired methotrexate elimination in adult and pediatric patients.
- the treatment of adults with metastatic colorectal cancer in combination with fluorouracil.

Limitations of Use:

Levoleucovorin injection is not indicated for pernicious anemia and megaloblastic anemia secondary to the lack of vitamin B12,because of the risk of progression of neurologic manifestations despite hematologic remission.

2 DOSAGE AND ADMINISTRATION

2.1 Important Use Information

Levoleucovorin injection is indicated for intravenous administration only . Do not administer intrathecally.

2.2 Co-administration of Levoleucovorin Injection with Other Agents

Due to the risk of precipitation, do not co-administer levoleucovorin injection with other agents in the same admixture.

2.3 Recommended Dosage for Rescue After High-Dose Methotrexate Therapy

The recommended dosage for levoleucovorin injection is based on a methotrexate dose of 12 grams/m^2administered by intravenous infusion over 4 hours. Twenty-four hours after starting the methotrexate infusion, initiate levoleucovorin injection at a dose of 7.5 mg (approximately 5 mg/m^2) as an intravenous infusion every 6 hours.

Monitor serum creatinine and methotrexate levels at least once daily. Continue levoleucovorin injection administration, hydration, and urinary alkalinization (pH of 7 or greater) until the methotrexate level is below 5 x 10^-8M (0.05 micromolar). Adjust the levoleucovorin injection dose or extend the duration as recommended in Table 1.

Table 1: Recommended Dosage for Levoleucovorin Injection based on Serum Methotrexate and Creatinine Levels
Clinical Situation | Laboratory Findings | Recommendation
Normal; Methotrexate; Elimination | Serum methotrexate level approximately 10 micromolar at 24 hours after administration, 1 micromolar at 48 hours, and less than 0.2 micromolar at 72 hours | Administer 7.5 mg by intravenous infusion every 6 hours for 60 hours (10 doses starting at 24 hours after start of methotrexate infusion).
Delayed Late; Methotrexate; Elimination | Serum methotrexate level remaining above 0.2 micromolar at 72 hours, and more than 0.05 micromolar at 96 hours after administration. | Continue 7.5 mg by intravenous infusion every 6 hours until methotrexate level is less than 0.05 micromolar.
Delayed Early; Methotrexate; Elimination and/or; Evidence of Acute; Renal Injury* | Serum methotrexate level of 50 micromolar or more at 24 hours, or 5 micromolar or more at 48 hours after administration; OR; 100% or greater increase in serum creatinine level at 24 hours after methotrexate administration (e.g., an increase from 0.5 mg/dL to a level of 1 mg/dL or more). | Administer 75 mg by intravenous infusion every 3 hours until methotrexate level is less than 1 micromolar; then 7.5 mg by intravenous infusion every 3 hours until methotrexate level is less than 0.05 micromolar.

* These patients are likely to develop reversible renal failure. In addition to appropriate levoleucovorin injection therapy, continue hydration and urinary alkalinization and monitor fluid and electrolyte status, until the serum methotrexate level has fallen to below 0.05 micromolar and the renal failure has resolved.

Impaired Methotrexate Elimination or Renal Impairment

Decreased methotrexate elimination or renal impairment which are clinically important but less severe than the abnormalities described in Table 1can occur following methotrexate administration. If toxicity associated with methotrexate is observed, in subsequent courses extend levoleucovorin injection rescue for an additional 24 hours (total of 14 doses over 84 hours).

Third-Space Fluid Collection and Other Causes of Delayed Methotrexate Elimination

Accumulation in a third space fluid collection (i.e., ascites, pleural effusion), renal insufficiency, or inadequate hydration can delay methotrexate elimination. Under such circumstances, higher doses of levoleucovorin injection or prolonged administration may be indicated.

2.4 Recommended Dosage for Overdosage of Folic Acid Antagonists or Impaired Methotrexate Elimination

Start levoleucovorin injection as soon as possible after an overdosage of methotrexate or within 24 hours of methotrexate administration when methotrexate elimination is impaired. As the time interval between methotrexate administration and levoleucovorin injection increases, the effectiveness of levoleucovorin injection to diminish methotrexate toxicity may decrease. Administer levoleucovorin injection 7.5 mg (approximately 5 mg/m^2) by intravenous infusion every 6 hours until the serum methotrexate level is less than 5 x 10^-8M (0.05 micromolar).

Monitor serum creatinine and methotrexate levels at least every 24 hours. Increase the dosage of levoleucovorin injection to 50 mg/m^2intravenously every 3 hours and continue levoleucovorin injection at this dosage until the methotrexate level is less than 5 x 10^-8M for the following:

- if serum creatinine at 24-hours increases 50% or more compared to baseline
- if the methotrexate level at 24-hours is greater than 5 x 10^-6M
- if the methotrexate level at 48-hours is greater than 9 x 10^-7M,

Continue concomitant hydration (3 L per day) and urinary alkalinization with sodium bicarbonate. Adjust the sodium bicarbonate dose to maintain urine pH at 7 or greater.

2.5 Dosage in Combination with Fluorouracil for Metastatic Colorectal Cancer

The following regimens have been used for the treatment of colorectal cancer:

- Levoleucovorin injection 100 mg/m^2by intravenous injection over a minimum of 3 minutes, followed by fluorouracil at 370 mg/m^2by intravenous injection, once daily for 5 consecutive days.
- Levoleucovorin injection 10 mg/m^2by intravenous injection, followed by fluorouracil 425 mg/m^2by intravenous injection, once daily for 5 consecutive days.

Administer fluorouracil and levoleucovorin injection separately to avoid the formation of a precipitate.

This five-day course may be repeated every 4 weeks for 2 courses, then every 4 to 5 weeks, if the patient has recovered from the toxicity from the prior course. Do not adjust levoleucovorin injection dosage for toxicity.

Refer to fluorouracil prescribing information for information on fluorouracil dosage and dosage modifications for adverse reactions.

2.6 Preparation for Administration

- Levoleucovorin contains no preservative. Observe strict aseptic technique during reconstitution of the drug product. Discard unused portion.
- Levoleucovorin solutions may be further diluted to concentrations of 0.5 mg per mL in 0.9% Sodium Chloride Injection, USP or 5% Dextrose Injection, USP. Do not store the product diluted using 0.9% Sodium Chloride Injection, USP or 5% Dextrose Injection, USP for more than 4 hours at room temperature.
- Visually inspect the diluted solution for particulate matter and discoloration prior to administration. Do not use if cloudiness or precipitate is observed.
- Inject no more than 16 mL of levoleucovorin injection (160 mg of levoleucovorin) intravenously per minute, because of the calcium content of the levoleucovorin solution.

3 DOSAGE FORMS AND STRENGTHS

- Injection: 175 mg/17.5 mL (10 mg/mL) or 250 mg/25 mL (10 mg/mL) of levoleucovorin sterile colorless to faint yellow solution in a single-dose vial.

4 CONTRAINDICATIONS

Levoleucovorin is contraindicated in patients who have had severe hypersensitivity to leucovorin products, folic acid or folinic acid [see Adverse Reactions (6.2)] .

5 WARNINGS AND PRECAUTIONS

5.1 Hypercalcemia

Because of the calcium content of the levoleucovorin solution, inject no more than 16 mL (160 mg of levoleucovorin) intravenously per minute.

5.2 Increased Gastrointestinal Toxicities with Fluorouracil

Leucovorin products increase the toxicities of fluorouracil [see Drug Interactions (7)] . Gastrointestinal toxicities, including stomatitis and diarrhea, occur more commonly and may be of greater severity and of prolonged duration. Deaths from severe enterocolitis, diarrhea, and dehydration have occurred in elderly patients receiving weekly d,l-leucovorin and fluorouracil.

Monitor patients for gastrointestinal toxicities. Do not initiate or continue therapy with levoleucovorin and fluorouracil in patients with symptoms of gastrointestinal toxicity until those symptoms have resolved. Monitor patients with diarrhea until resolved, as rapid deterioration leading to death can occur.

5.3 Drug Interaction with Trimethoprim-Sulfamethoxazole

The concomitant use of d,l-leucovorin with trimethoprim-sulfamethoxazole for the acute treatment of Pneumocystis jiroveci pneumonia in patients with HIV infection was associated with increased rates of treatment failure and morbidity [see Drug Interactions (7)] .

6 ADVERSE REACTIONS

The following clinically significant adverse reactions are described elsewhere in the labeling:

- Hypercalcemia [see Warnings and Precautions (5.1)]
- Increased gastrointestinal toxicities with fluorouracil [see Warnings and Precautions (5.2)]

6.1 Clinical Trials Experience

Because clinical trials are conducted under widely varying conditions, adverse reaction rates observed in the clinical trials of a drug cannot be directly compared to rates in the clinical trials of another drug and may not reflect the rates observed in practice.

High-Dose Methotrexate Therapy

Table 2presents the frequency of adverse reactions which occurred during the administration of 58 courses of high-dose methotrexate 12 grams/m^2followed by levoleucovorin rescue for osteosarcoma in 16 patients aged 6 to 21 years. Most patients received levoleucovorin 7.5 mg every 6 hours for 60 hours or longer, beginning 24 hours after completion of methotrexate administration.

Table 2 Adverse Reactions with High-Dose Methotrexate Therapy
Adverse Reactions | Levoleucovorin n = 16
Adverse Reactions | All Grades (%) | Grades 3-4 (%)
Gastrointestinal
Stomatitis | 38 | 6
Vomiting | 38 | 0
Nausea | 19 | 0
Diarrhea | 6 | 0
Dyspepsia | 6 | 0
Typhlitis | 6 | 6
Respiratory
Dyspnea | 6 | 0
Skin and Appendages
Dermatitis | 6 | 0
Other
Confusion | 6 | 0
Neuropathy | 6 | 0
Renal function abnormal | 6 | 0
Taste perversion | 6 | 0

Combination with Fluorouracil in Colorectal Cancer

Table 3presents the frequency of adverse reaction which occurred in 2 arms of a randomized controlled trial conducted by the North Central Cancer Treatment Group (NCCTG) in patients with metastatic colorectal cancer. The trial failed to show superior overall survival with fluorouracil + levoleucovorin compared to fluorouracil + d,l-leucovorin. Patients were randomized to fluorouracil 370 mg/m^2intravenously and levoleucovorin 100 mg/m^2intravenously, both daily for 5 days, or to fluorouracil 370 mg/m^2intravenously and d,l-leucovorin 200 mg/m^2intravenously, both daily for 5 days. Treatment was repeated week 4 and week 8, and then every 5 weeks until disease progression or unacceptable toxicity.

Table 3 Adverse Reactions Occurring in ≥ 10% of Patients in Either Arm
Adverse Reaction | Levoleucovorin/fluorouracil n=318 |  | d,l-Leucovorin/fluorouracil n=307
Adverse Reaction | Grades 1-4 (%) | Grades 3-4; (%) | Grades 1-4 (%) | Grades 3-4 (%)
Gastrointestinal Disorders
Stomatitis | 72 | 12 | 72 | 14
Diarrhea | 70 | 19 | 65 | 17
Nausea | 62 | 8 | 61 | 8
Vomiting | 40 | 5 | 37 | 6
Abdominal Pain^1 | 14 | 3 | 19 | 3
General Disorders
Asthenia/Fatigue/Malaise | 29 | 5 | 32 | 11
Skin Disorders
Dermatitis | 29 | 1 | 28 | 1
Alopecia | 26 | 0.3 | 28 | 1
Metabolism and Nutrition
Anorexia/Decreased Appetite | 24 | 4 | 25 | 2
^1Includes abdominal pain, upper abdominal pain, lower abdominal pain, and abdominal tenderness

6.2 Postmarketing Experience

The following adverse reaction have been identified during postapproval use of levoleucovorin products. Because these reactions are reported from a population of uncertain size, it is not always possible to reliably estimate their frequency or establish a causal relationship to drug exposure.

Dermatologic:pruritus, rash

Respiratory:dyspnea

Other:temperature change, rigors, allergic reactions

7 DRUG INTERACTIONS

7.1 Effects of Leucovorin Products on Other Drugs

Antiepileptic Drugs

Folic acid in large amounts may counteract the antiepileptic effect of phenobarbital, phenytoin and primidone and increase the frequency of seizures in susceptible children. It is not known whether folinic acid has the same effects; however, both folic and folinic acids share some common metabolic pathways. Monitor patients taking folinic acid in combination with antiepileptic drugs.

Fluorouracil

Leucovorin products increase the toxicity of fluorouracil. Do not initiate or continue therapy with levoleucovorin and fluorouracil in patients with symptoms of gastrointestinal toxicity until those symptoms have resolved. Monitor patients with diarrhea until the diarrhea has resolved, as rapid deterioration leading to death can occur [see Warnings and Precautions (5.2)].

Trimethoprim-Sulfamethoxazole

The concomitant use of d,l-leucovorin with trimethoprim-sulfamethoxazole for the acute treatment of Pneumocystisjiroveci pneumonia in patients with HIV infection was associated with increased rates of treatment failure and morbidity in a placebo-controlled study [see Warnings and Precautions (5.3)] .

8 USE IN SPECIFIC POPULATIONS

8.1 Pregnancy

Risk Summary

There are limited data with levoleucovorin use in pregnant women. Animal reproduction studies have not been conducted with levoleucovorin.

Levoleucovorin is administered in combination with methotrexate or fluorouracil, which can cause embryo-fetal harm. Refer to methotrexate and fluorouracil prescribing information for additional information.

In the U.S. general population, the estimated background risk of major birth defects and miscarriage in clinically recognized pregnancies is 2% to 4% and 15% to 20%, respectively.

8.2 Lactation

Risk Summary

There are no data on the presence of levoleucovorin in human milk or its effects on the breastfed infant or on milk production.

Levoleucovorin is administered in combination with methotrexate or fluorouracil. Refer to methotrexate and fluorouracil prescribing information for additional information.

8.4 Pediatric Use

The safety and effectiveness of levoleucovorin have been established in pediatric patients for rescue after high-dose methotrexate therapy in osteosarcoma and diminishing the toxicity associated with overdosage of folic acid antagonists or impaired methotrexate elimination. Use of levoleucovorin in pediatric patients is supported by open-label clinical trial data in 16 pediatric patients 6 years of age and older, with additional supporting evidence from literature [see Clinical Studies (14.1)].

The safety and effectiveness of levoleucovorin have not been established for the treatment of pediatric patients with advanced metastatic colorectal cancer.

8.5 Geriatric Use

Clinical studies of levoleucovorin in the treatment of osteosarcoma did not include patients aged 65 and over to determine whether they respond differently from younger patients.

In the NCCTG clinical trial of levoleucovorin in combination with fluorouracil for the treatment of metastatic colorectal cancer, no overall differences in safety or effectiveness were observed between patients age 65 years and older and younger patients.

11 DESCRIPTION

Levoleucovorin is a folate analog and the pharmacologically active levo-isomer of d,l-leucovorin. The chemical name of levoleucovorin calcium is calcium (6S)-N-{4-[[(2-amino-5-formyl-1,4,5,6,7,8-hexahydro-4-oxo-6-pteridinyl)methyl] amino]benzoyl}-L-glutamate mixed hydrates. The molecular formula is C20H21CaN7O7●nH2O (n = 3.2 to 5.8) and the molecular weight is 569.1 to 616.0. The molecular structure is:

Levoleucovorin injection, for intravenous use is supplied as a colorless to faint yellow solution of either 175 mg levoleucovorin in 17.5 mL or 250 mg levoleucovorin in 25 mL per single-dose vial. Each mL contains 10 mg levoleucovorin (equivalent to 10.8 mg levoleucovorin calcium (as mixed hydrates)) and 8.3 mg sodium chloride. Sodium hydroxide is used for pH adjustment to pH 8.2 (6.5 to 8.5).

12 CLINICAL PHARMACOLOGY

12.1 Mechanism of Action

High-Dose Methotrexate Therapy

Levoleucovorin is the pharmacologically active isomer of 5-formyl tetrahydrofolic acid. Levoleucovorin does not require reduction by the enzyme dihydrofolate reductase in order to participate in reactions utilizing folates as a source of “one-carbon” moieties. Administration of levoleucovorin counteracts the therapeutic and toxic effects of folic acid antagonists such as methotrexate, which act by inhibiting dihydrofolate reductase.

Combination with Fluorouracil in Colorectal Cancer

Levoleucovorin enhances the therapeutic and toxic effects of fluorouracil. Fluorouracil is metabolized to 5-fluoro-2'-deoxyuridine-5'-monophosphate (FdUMP), which binds to and inhibits thymidylate synthase (an enzyme important in DNA repair and replication). Levoleucovorin is converted to another reduced folate, 5,10-methylenetetrahydrofolate, which acts to stabilize the binding of FdUMP to thymidylate synthase and thereby enhancing the inhibition of thymidylate synthase.

12.3 Pharmacokinetics

The pharmacokinetics of levoleucovorin after intravenous administration of a 15 mg dose was studied in healthy subjects. The mean maximum serum total tetrahydrofolate (total-THF) concentrations was 1722 ng/mL (CV 39%) and the mean maximum serum (6S)-5-methyl-5,6,7,8-tetrahydrofolate concentrations was 275 ng/mL (CV 18%) observed around 0.9 hours post injection.

Distribution

Exploratory studies show that small quantities of systemically administered leucovorin enter the cerebrospinal fluid (CSF), primarily as its major metabolite 5-methyltetrahydrofolate (5-MTHFA). In humans, the CSF levels of 5-MTHFA remain 1-3 orders of magnitude lower than the usual methotrexate concentrations following intrathecal administration.

Elimination

The mean terminal half-life was 5.1 hours for total-THF and 6.8 hours for (6S)-5-methyl-5,6,7,8-tetrahydrofolate.

Drug Interaction Studies

The mean dose-normalized steady-state plasma concentrations for both levoleucovorin and 5-methyl-THF were comparable whether fluorouracil (370 mg/m^2/day as an intravenous bolus) was given in combination with levoleucovorin (250 mg/m^2and 1000 mg/m^2as a continuous intravenous infusion for 5.5 days) or with d,l-leucovorin (500 mg/m^2as a continuous intravenous infusion for 5.5 days).

13 NONCLINICAL TOXICOLOGY

13.1 Carcinogenesis, Mutagenesis, Impairment of Fertility

No studies have been conducted to evaluate the potential of levoleucovorin for carcinogenesis, mutagenesis and impairment of fertility.

14 CLINICAL STUDIES

14.1 Rescue after High-Dose Methotrexate Therapy in Patients with Osteosarcoma

The efficacy of levoleucovorin rescue following high-dose methotrexate was evaluated in 16 patients aged 6 to 21 years who received 58 courses of therapy for osteogenic sarcoma. High-dose methotrexate was one component of several different combination chemotherapy regimens evaluated across several trials. Methotrexate 12 grams/m^2as an intravenous infusion over 4 hours was administered to 13 patients, who received levoleucovorin 7.5 mg by intravenous infusion every 6 hours for 60 hours or longer beginning 24 hours after completion of methotrexate. Three patients received methotrexate 12.5 grams/m^2intravenously over 6 hours, followed by levoleucovorin 7.5 mg by intravenous infusion every 3 hours for 18 doses beginning 12 hours after completion of methotrexate. The mean number of levoleucovorin doses per course was 18.2 and the mean total dose per course was 350 mg. The efficacy of levoleucovorin rescue following high-dose methotrexate was based on the adverse reaction profile [see Adverse Reactions (6.1)].

14.2 Metastatic Colorectal Cancer

In a randomized clinical study conducted by Mayo Clinic and North Central Cancer Treatment Group (NCCTG) in patients with metastatic colorectal cancer comparing d,l-leucovorin 200 mg/m^2and fluorouracil 370 mg/m^2versus d,l-leucovorin 20 mg/m^2and fluorouracil 425 mg/m^2versus fluorouracil 500 mg/m^2, with all drugs administered by intravenous infusion daily for 5 days every 28 to 35 days, response rates were 26% (p=0.04 versus fluorouracil alone), 43% (p=0.001 versus fluorouracil alone) and 10%, respectively. Respective median survival times were 12.2 months (p=0.037), 12 months (p=0.050), and 7.7 months. The low dose d,l-leucovorin regimen was associated with a statistically significant improvement in weight gain of more than 5%, relief of symptoms, and improvement in performance status. The high dose d,l-leucovorin regimen was associated with a statistically significant improvement in performance status and trended toward improvement in weight gain and in relief of symptoms but these were not statistically significant.

In a second randomized clinical study conducted by Mayo Clinic and NCCTG, the fluorouracil alone arm was replaced by a regimen of sequentially administered methotrexate, fluorouracil, and d,l-leucovorin. Response rates with d,l-leucovorin 200 mg/m^2and fluorouracil 370 mg/m^2versus d,l-leucovorin 20 mg/m^2and fluorouracil 425 mg/m^2versus sequential methotrexate and fluorouracil and d,l-leucovorin were respectively 31% (p≤0.01), 42% (p≤0.01), and 14%. Respective median survival times were 12.7 months (p≤0.04), 12.7 months (p≤0.01), and 8.4 months. There was no statistically significant difference in weight gain of more than 5% or in improvement in performance status was seen between the treatment arms.

A randomized controlled trial conducted by NCCTG in patients with metastatic colorectal cancer failed to show superiority of a regimen of fluorouracil + levoleucovorin to fluorouracil + d,l-leucovorin in overall survival. Patients were randomized to fluorouracil 370 mg/m^2intravenously and levoleucovorin 100 mg/m^2intravenously, both daily for 5 days, or to fluorouracil 370 mg/m^2intravenously and d,l-leucovorin 200 mg/m^2intravenously, both daily for 5 days. Treatment was repeated week 4 and week 8, and then every 5 weeks until disease progression or unacceptable toxicity.

16 HOW SUPPLIED/STORAGE AND HANDLING

Levoleucovorin injection is a sterile colorless to faint yellow solution in a single-dose vial available as:

175 mg/17.5 mL (10 mg/mL) solution – NDC 70436-209-80

250 mg/25 mL (10 mg/mL) solution – NDC 70436-210-80

Store in refrigerator at 2°C to 8°C (36°F to 46°F). Protect from light. Store in carton until contents are used.

Manufactured by:

Hainan Poly Pharm. Co., Ltd.

Hainan Province, China, 571127

Distributed by:

Slate Run Pharmaceuticals, LLC

Columbus, Ohio 43215

Package/Label Display Panel

70436-209-80

Package/Label Display Panel

70436-210-80